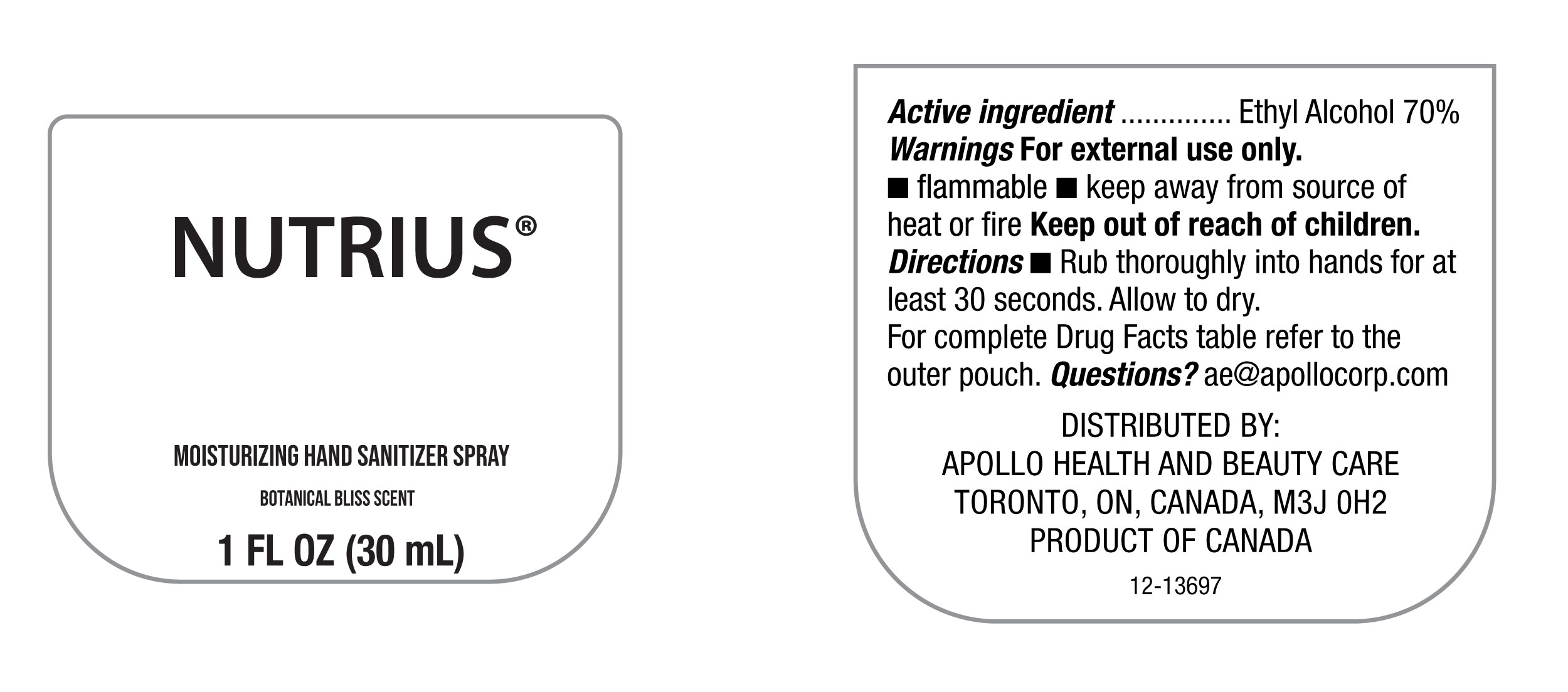 DRUG LABEL: Hand Sanitizer
NDC: 63148-124 | Form: SPRAY
Manufacturer: Apollo Health and Beauty Care
Category: otc | Type: HUMAN OTC DRUG LABEL
Date: 20260114

ACTIVE INGREDIENTS: ALCOHOL 70 mL/100 mL
INACTIVE INGREDIENTS: WATER; TRIS(TETRAMETHYLHYDROXYPIPERIDINOL) CITRATE; ISOPROPYL MYRISTATE; GLYCERIN; RED 4; FRAGRANCE CLEAN ORC0600327; .ALPHA.-TOCOPHEROL ACETATE; VIOLET 2; ISOPROPYL ALCOHOL; ALOE VERA LEAF

NDC-63148-124.- Botanical Bliss Scent

Active Ingredient

Ethyl Alcohol-70%

Purpose

Antiseptic

Uses

For Personal Hygiene to help prevent the spread of bacteria and can be used in place of hand washing if soap and water are not available.

Warnings

For external use only

- Flammable
- Keep away from source of heat or fire.

Do not use

- On infants less than 2 months of age.
- On open skin wounds.
- On broken or damaged skin.

When using this product avoid.

- Contact with eyes. If contact occurs, rinse eyes throughly with water.
- Do not inhale.

Stop use and ask a doctor.

If irritation or redness develops and lasts.

Keep out of reach of children.

In case of accidental ingestion, get medical help or contact a Poison Control Center immediately

Directions

For Occassional andPersonal use.

Rub thoroughly into hands for at least 30 seconds. Allow to dry.

Children under 6 years should be supervised when using the product.

Inactive Ingredients

Aloe Barbadensis Leaf Powder, Ext. Violet 2 (Cl 60730), Fragrance (Parfum), Glycerin, Isopropyl Alcohol, Isopropyl Myristate, Red 4 (CI 14700), Tocopheryl Acetate, Tris(Tetramethylhydroxypiperidinol) Citrate, Water (Aqua).

Questions

ae@apollocorp.com